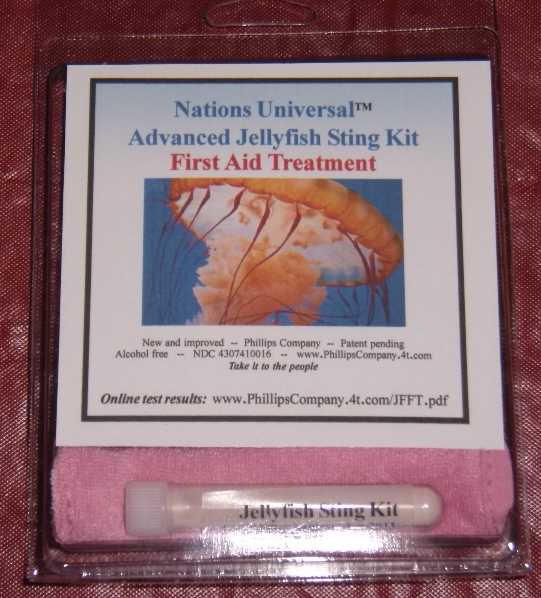 DRUG LABEL: Advanced Jellyfish Sting Kit
NDC: 43074-114 | Form: POWDER, FOR SUSPENSION
Manufacturer: Phillips Company
Category: otc | Type: HUMAN OTC DRUG LABEL
Date: 20101112

ACTIVE INGREDIENTS: zinc acetate 0.001 mg/1 mL
INACTIVE INGREDIENTS: dimethyl sulfoxide; ascorbic acid; dipropylene glycol; water; sorbic acid; magnesium stearate; stearic acid; sodium dodecylbenzenesulfonate; calcium carbonate; sodium carbonate; sodium hypochlorite

DRUG FACTS

DRUG FACTS

Uses
Temporarily protects injured or exposed skin or mucous membrane surfaces from harmful or annoying stimuli, and may help provide relief to such surfaces. Contains surfactants to break down oily toxins.
____________________________________________________________________
Warnings
n For external use only; do not swallow. n Keep away from children.
n Do not use in the eyes or apply over large areas of the body.
n Do not use if allergic to any ingredient listed on this label.
____________________________________________________________________
Directions
Step 1: Wet the skin with water and apply powder to the affected area. Step 2: Use water to wet the special cloth and use it to scrub the affected area to remove jellyfish barbs and to mix the protectant with any remaining toxins. Step 3: Repeat Steps 1 and 2 a minimum of three times or until stinging and pain stops. Step 4: Seek immediate medical attention.
____________________________________________________________________
Other information
Store at 40 to 120 degrees F. Net contents of kit: One special scrub cloth and one powder vial. Net contents of powder vial: 3 mL. This product contains no alcohol; no animal products; no biological products.
____________________________________________________________________
Inactive ingredients
Water, calcium carbonate, sodium hypochlorite, sodium carbonate, sodium dodecylbenzene sulfonate, ascorbic acid, magnesium stearate, sorbic acid, stearic acid, diproplyene glycol, dimethyl sulfoxide, color.
____________________________________________________________________
Questions and Side effects
Report any side effects to Phillips Company, 311 Chickasaw St, Millerton, OK USA 74750
Email: phillips@123phillips.com

ACTIVE INGREDIENTS

Active Ingredients Purpose
Zinc acetate (.1% by volume) Skin Protectant

ASK DOCTOR

Directions
Step 1: Wet the skin with water and apply powder to the affected area. Step 2: Use water to wet the special cloth and use it to scrub the affected area to remove jellyfish barbs and to mix the protectant with any remaining toxins. Step 3: Repeat Steps 1 and 2 a minimum of three times or until stinging and pain stops. Step 4: Seek immediate medical attention.

DO NOT USE

Warnings
n For external use only; do not swallow. n Keep away from children.
n Do not use in the eyes or apply over large areas of the body.
n Do not use if allergic to any ingredient listed on this label.

CHILDREN

n Keep away from children.
n Do not use in the eyes or apply over large areas of the body.
n Do not use if allergic to any ingredient listed on this label.

PURPOSE

Active Ingredients Purpose
Zinc acetate (.1% by volume) Skin Protectant

WHEN USING

Directions
Step 1: Wet the skin with water and apply powder to the affected area. Step 2: Use water to wet the special cloth and use it to scrub the affected area to remove jellyfish barbs and to mix the protectant with any remaining toxins. Step 3: Repeat Steps 1 and 2 a minimum of three times or until stinging and pain stops. Step 4: Seek immediate medical attention.

Store at 40 to 120 degrees F.

WARNINGS

n For external use only; do not swallow. n Keep away from children.
n Do not use in the eyes or apply over large areas of the body.
n Do not use if allergic to any ingredient listed on this label.

DOSAGE & ADMINISTRATION

Directions
Step 1: Wet the skin with water and apply powder to the affected area. Step 2: Use water to wet the special cloth and use it to scrub the affected area to remove jellyfish barbs and to mix the protectant with any remaining toxins. Step 3: Repeat Steps 1 and 2 a minimum of three times or until stinging and pain stops. Step 4: Seek immediate medical attention.

USE

Temporarily protects injured or exposed skin or mucous membrane surfaces from harmful or annoying stimuli, and may help provide relief to such surfaces. Contains surfactants to break down oily toxins.

INACTIVE INGREDIENTS

Water, calcium carbonate, sodium hypochlorite, sodium carbonate, sodium dodecylbenzene sulfonate, ascorbic acid, magnesium stearate, sorbic acid, stearic acid, diproplyene glycol, dimethyl sulfoxide, color.

Image of product